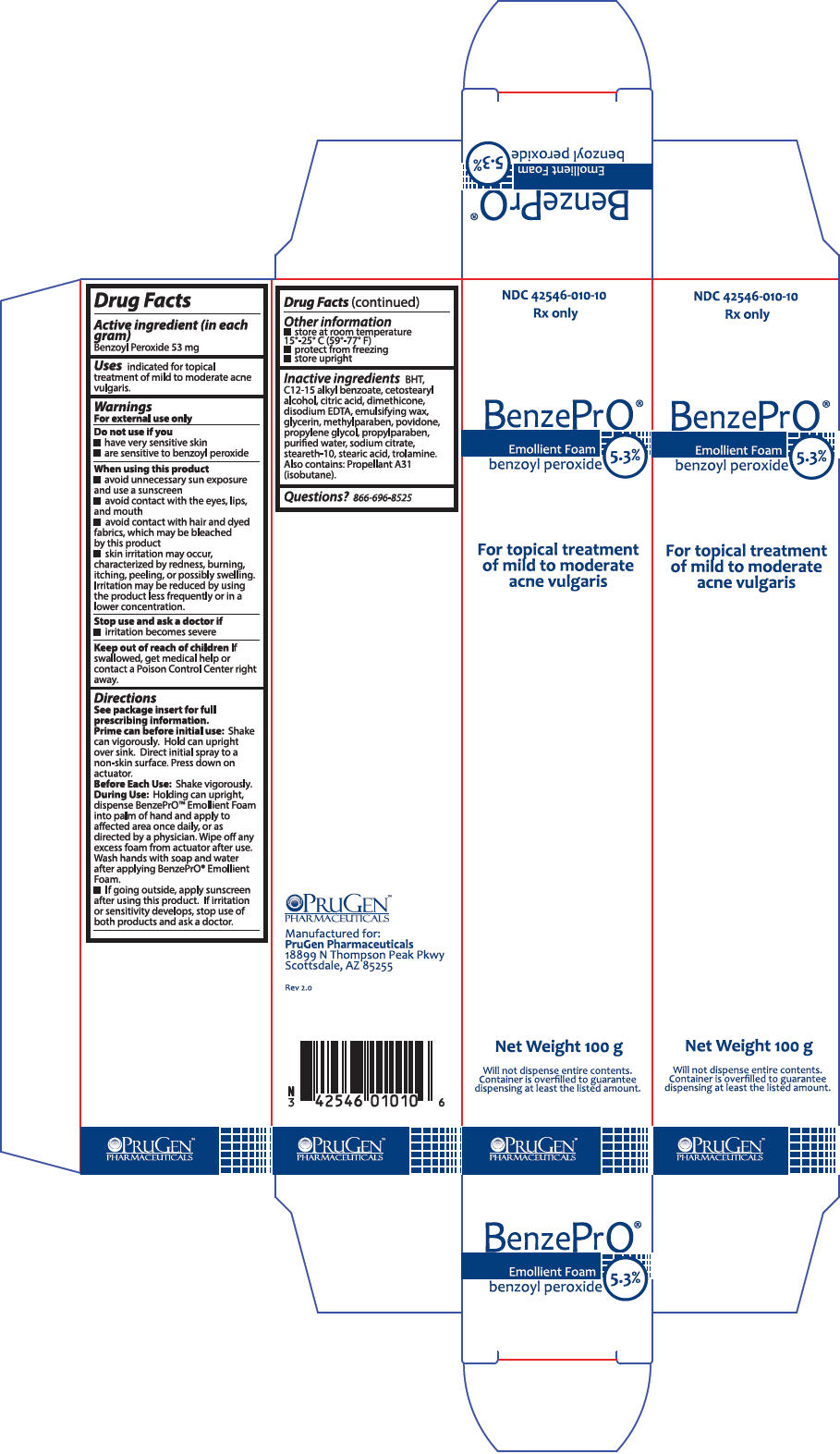 DRUG LABEL: BenzePrO
NDC: 42546-010 | Form: AEROSOL, FOAM
Manufacturer: PruGen, Inc.
Category: otc | Type: HUMAN OTC DRUG LABEL
Date: 20180620

ACTIVE INGREDIENTS: BENZOYL PEROXIDE 3.18 g/60 g
INACTIVE INGREDIENTS: BUTYLATED HYDROXYTOLUENE; ALKYL (C12-15) BENZOATE; CETOSTEARYL ALCOHOL; CITRIC ACID MONOHYDRATE; DIMETHICONE; EDETATE DISODIUM; GLYCERIN; METHYLPARABEN; POVIDONE, UNSPECIFIED; PROPYLENE GLYCOL; PROPYLPARABEN; WATER; SODIUM CITRATE, UNSPECIFIED FORM; STEARETH-10; STEARIC ACID; TROLAMINE

BenzePro Emollient Foam

BenzePrO™ Emollient Foam

Drug Facts

Active ingredients

Benzoyl Peroxide 5.3%

Purpose

Acne Treatment

Uses

Indicated for the topical treatment of mild to moderate acne vulgaris

Warnings

For external use only

Do not use if you

- have very sensitive skin
- are sensitive to Benzoyl Peroxide

When using this product

- avoid unnecessary sun exposure and use a sunscreen
- avoid contact with eyes, lips, and mouth
- avoid contact with hair and dyed fabrics, which may be bleached by this product
- skin irritation may occur, characterized by redness, burning, itching, peeling, possibly swelling. Irritation may be reduced by using the product less frequently or in a lower concentration

Stop and ask a doctor if

- irritation becomes severe

Keep out of reach of children.

If swallowed, get medical help or contact a Poison Control Center right away.

Directions

See package insert for full prescribing information

Prime can before initial use: See package insert Before Each Use: Shake vigorously

During Use: Holding can upright, dispense into palm of hand and apply to affected area as directed by physician.

- If going outside, apply sunscreen after using this product. If irritation or sensitivity develops, stop use of both products and ask a doctor.

Other Information

- Store at room temperature 15°-25° C (59°-77° F)
- Protect from freezing
- Store upright

Inactive Ingredients

BHT, C12-15 alkyl benzoate, cetostearyl alcohol, citric acid, dimethicone, disodium EDTA, emulsifying wax, glycerin, methylparaben, povidone, propylene glycol, propylparaben, purified water, sodium citrate, steareth-10, stearic acid, trolamine. Also contains: Propellant HFA-134A (1, 1, 1, 2-tetrafluoroethane).

Questions? 866-696-8525

Manufactured for:
PruGen, Inc.
Pharmaceuticals
18899 North Thompson Peak Parkway
Scottsdale, Arizona 85255 REV 1.2

PRINCIPAL DISPLAY PANEL - 100 g Can Box

NDC 42546-010-10
Rx only

BenzePrO®

Emollient Foam
benzoyl peroxide
5.3%

For topical treatment
of mild to moderate
acne vulgaris

Net Weight 100 g

Will not dispense entire contents.
Container is overfilled to guarantee
dispensing at least the listed amount.

PRUGEN™
PHARMACEUTICALS